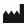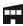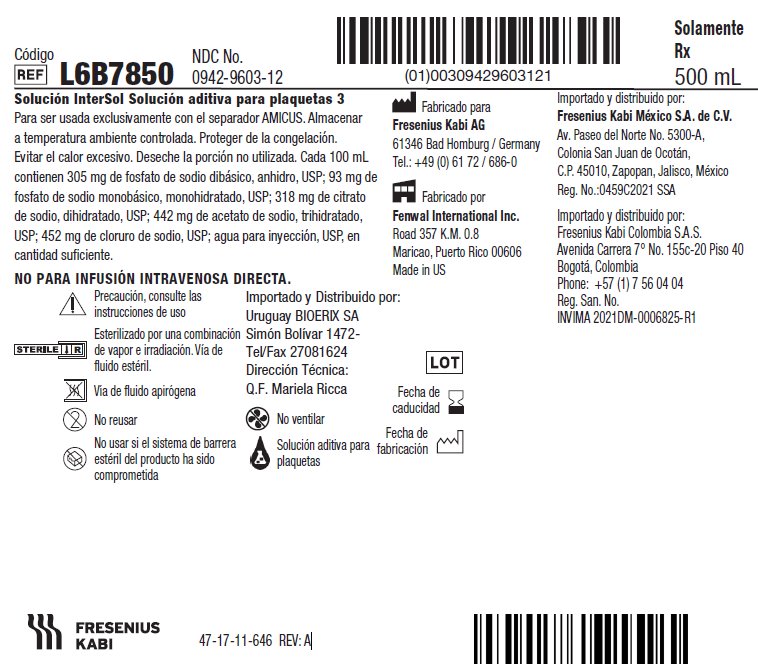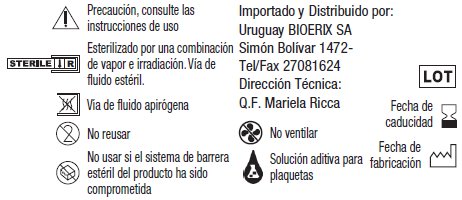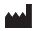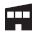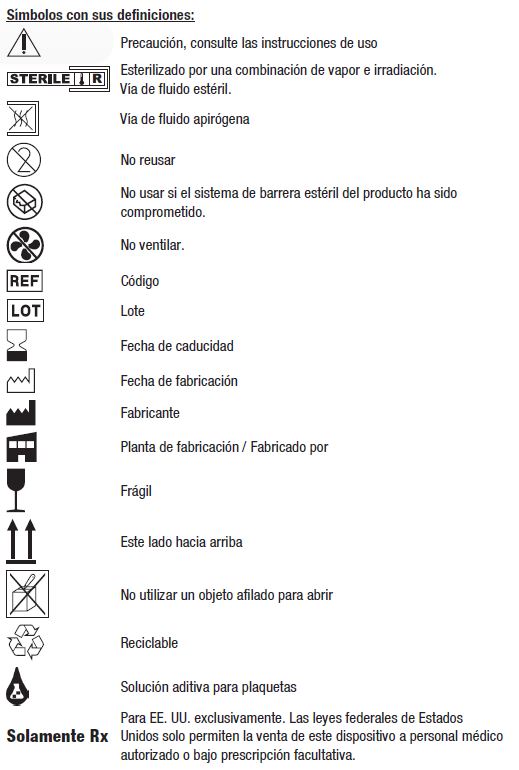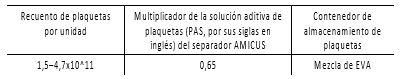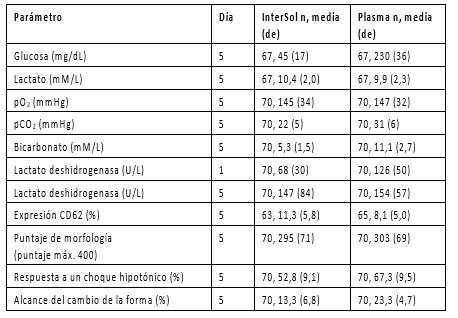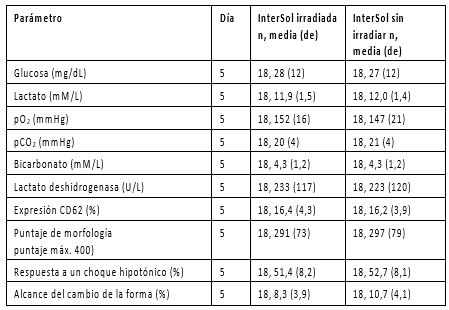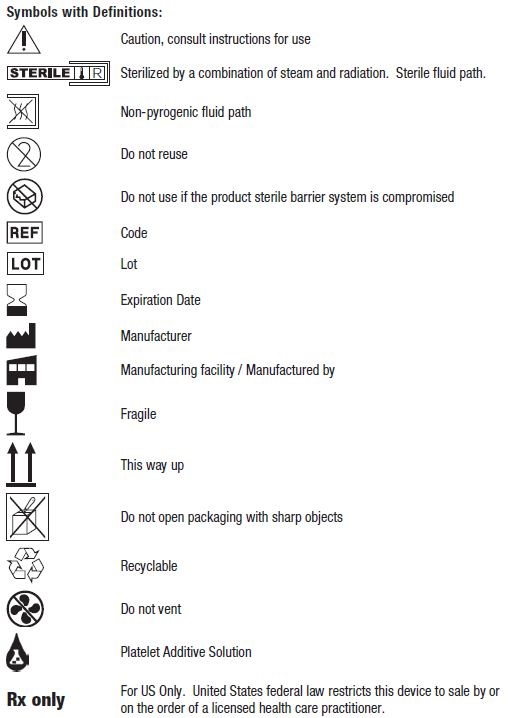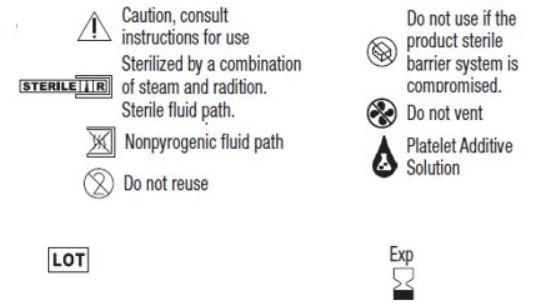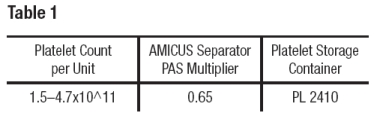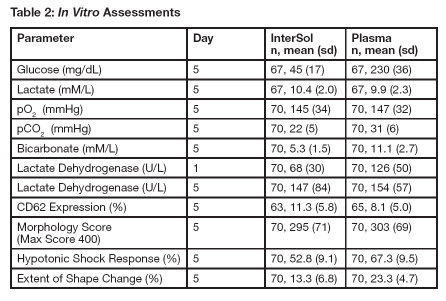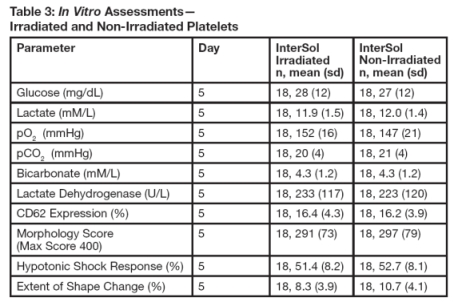 DRUG LABEL: Solucion InterSol
NDC: 0942-9603 | Form: SOLUTION
Manufacturer: Fenwal, Inc.
Category: prescription | Type: HUMAN PRESCRIPTION DRUG LABEL
Date: 20211004

ACTIVE INGREDIENTS: Sodium Chloride 452 mg/100 mL; SODIUM ACETATE 442 mg/100 mL; Trisodium Citrate Dihydrate 318 mg/100 mL; SODIUM PHOSPHATE, DIBASIC, UNSPECIFIED FORM 305 mg/100 mL; Sodium Phosphate, Monobasic, Monohydrate 93 mg/100 mL
INACTIVE INGREDIENTS: Water

Direction Insert

Spanish Language

Solución InterSol Solución aditiva para plaquetas 3
500 mL
Solamente Rx
Para ser usada exclusivamente con el separador AMICUS.
Almacenar a temperatura ambiente controlada. Proteger de la congelación. Evitar el calor excesivo.
Definición de "Temperatura ambiente controlada":
"Una temperatura mantenida termostáticamente entre 20 °C y 25 °C (68 °F y 77 °F) prevalente por lo general en el ambiente habitual de trabajo, la cual resulta en una temperatura cinética media calculada de no más de 25 °C, y que permite desviaciones de entre 15 °C y 30 °C (59 °F y 86 °F) experimentadas en farmacias, hospitales y almacenes. Se permiten elevaciones pasajeras de temperatura no superiores a los 40 °C, siempre que la temperatura cinética media permanezca en el intervalo permitido y que dichas elevaciones no duren más de 24 horas... La temperatura cinética media es un valor calculado que puede emplearse como la temperatura de almacenamiento isotérmica que simula los efectos no isotérmicos de las variaciones de temperatura de almacenamiento."
Referencia: United States Pharmacopeia, Avisos generales. United States Pharmacopeial Convention, Inc. 12601 Twinbrook Parkway, Rockville, MD.
Desechar los desperdicios en un contenedor apropiado de biopeligrosos o según los requisitos de regulaciones locales.
Indicaciones y uso:
La solución InterSol es una solución isotónica diseñada para sustituir una parte del plasma utilizado en el almacenamiento de plaquetas de aféresis leucorreducidas derivadas de AMICUS en las condiciones estándar de los bancos de sangre. No existe ningún efecto terapéutico directo derivado de la fórmula. La solución nunca se debe infundir directamente en el paciente.
Las plaquetas de InterSol son concentrados de plaquetas de aféresis leucorreducidas que se almacenan en una solución que, nominalmente, contiene 65% de InterSol y 35% de plasma. Las plaqueta de InterSol que se preparan dentro del intervalo indicado en la Tabla 1 pueden almacenarse por hasta 5 días a entre 20 y 24 °C, con agitación continua.
Tabla 1

Dosis y administración:
La solución InterSol solo se puede usar con el sistema separador AMICUS utilizando un kit de aféresis AMICUS con un conector de la solución aditiva de plaquetas (PAS). Para obtener instrucciones completas sobre el uso de la solución InterSol con el separador AMICUS, consulte el Manual del operador de AMICUS.
Antes de usar la solución InterSol, verificar que el contenedor plástico no tenga fugas apretando la bolsa con firmeza. Si existen fugas, desechar la solución.
Para conectar la solución InterSol al kit de aféresis AMICUS:
1) Cerrar la abrazadera de la línea del conector de PAS.
2) Retirar la tapa protectora del puerto de membrana en el contenedor de solución InterSol.
3) Introducir la espiga en la línea del conector de PAS hacia dentro del puerto que tiene una membrana en el contenedor de solución InterSol hasta que quede bien asentada.
4) Para agregar solución InterSol al producto de plaquetas, seguir las instrucciones incluidas en el Manual del operador de AMICUS.
Presentaciones y concentraciones de la dosis:
La solución InterSol viene en la forma de 500 mL de solución apirogéna esterilizada en un contenedor plástico que no es de PVC y que incluye una vía de fluido apirogéna esterilizada.
Cada 100 mL contienen 305 mg de fosfato de sodio dibásico, anhidro, USP; 93 mg de fosfato de sodio monobásico, monohidratado, USP; 318 mg de citrato de sodio, dihidratado, USP; 442 mg de acetato de sodio, trihidratado, USP; 452 mg de cloruro de sodio, USP; agua para inyección, USP, en cantidad suficiente.
Contraindicaciones:
La solución InterSol se añade a los concentrados de plaquetas leucorreducidas derivadas de AMICUS después de haber completado el proceso de aféresis. No es para infusión intravenosa directa. Se desconoce que existan contraindicaciones asociadas con el uso de la solución InterSol para la preparación de plaquetas InterSol.
Advertencias y precauciones:
• Solución InterSol NO ES PARA INFUSIÓN INTRAVENOSA DIRECTA.
• No utilizar si existen partículas o si la solución está turbia.
• No usar si el contenedor está dañado, tiene fugas o muestra signos de deterioro.
• No ventilar.
• No volver a usar. Desechar la solución InterSol parcialmente usada o sin usar.
• Proteger contra objetos puntiagudos.
• Comprobar que la solución InterSol se haya acoplado firmemente a la línea del conector PAS a fin de evitar desconexiones y fugas.
Reacciones adversas:
La solución InterSol se añade a los concentrados de plaquetas leucorreducidas derivadas de AMICUS después de haber completado el proceso de aféresis. No es para infusión intravenosa directa. No es de esperarse que la solución InterSol cause reacciones adversas más allá de las que normalmente están asociadas con la transfusión de plaquetas.
Abuso / dependencia de drogas:
La solución InterSol se utiliza como una solución de almacenamiento para los concentrados de plaquetas y no tiene efectos farmacológicos.
Sobredosis:
La solución InterSol se utiliza como una solución de almacenamiento para los concentrados de plaquetas y no es para infusión intravenosa directa.
Descripción:
La solución InterSol es una solución isotónica diseñada para reemplazar una parte del plasma utilizado en el almacenamiento de plaquetas. La solución contiene elementos constituyentes que son de existencia natural y que están presentes en muchos sistemas celulares: acetato de sodio, que actúa como nutriente; citrato de sodio para evitar la activación y la aglomeración de plaquetas; fosfato de sodio que actúa como buffer; y cloruro de sodio para efectos de osmolaridad. La solución InterSol no tiene un efecto farmacológico “in vivo”, sino que tiene la función de proporcionar el entorno y los nutrientes adecuados que sustituyen una parte del plasma que se utiliza normalmente para el almacenamiento de las plaquetas.
Farmacología clínica:
La solución InterSol se utiliza como una solución de almacenamiento para los concentrados de plaquetas y no es para infusión intravenosa directa. Esta solución no tiene efectos farmacológicos.
Estudios clínicos:
Evaluaciones funcionales y bioquímicas "in vitro"
Los concentrados de plaquetas con InterSol (n=70) que se prepararon utilizando el separador AMICUS y se han almacenado por 5 días exhibieron, en el día 5, un pH cuyos valores de media y valor promedio fueron, respectivamente, 7,2 y 7,2 ± 0,1 (el rango fue de 6,9 a 7,5), con un límite inferior no paramétrico de 6,9 con una tolerancia de 95%/95%.
En la Tabla 2 se presentan evaluaciones complementarias "in vitro" de plaquetas con InterSol y de plaquetas leucorreducidas derivadas de AMICUS que están almacenadas en plasma al 100%.
Se realizó una comparación entre plaquetas con InterSol no irradiadas y plaquetas con InterSol irradiadas (n=18) a 2500 cGray o a 2800 cGray (dependiendo de los procedimientos de la institución). Al final del almacenamiento, en el día 5, la producción de plaquetas de los productos irradiados fue de concentrados de entre 2,5 x 10^11 y 3,5 x 10^11 e incluyó un producto con una concentración <2,5 x 10^11 y dos productos con concentraciones >3,5 x 10^11. Las pruebas realizadas “in vitro” no predicen el rendimiento “in vivo”, pero esto no fue evaluado. En la Tabla 3 se presenta el resumen de los datos estadísticos.
Recuperación y supervivencia "in vivo" en sujetos sanos
La evaluación "in vivo" de plaquetas con InterSol en el día 5 (n=33), en comparación con un control con plaquetas nuevas dio como resultado una recuperación porcentual promedio de 46,4 ± 11,9 por ciento y 58,0 ± 10,7 por ciento y una supervivencia promedio de 5,7 ± 1,4 días y 8,0 ± 1,4 días, respectivamente. Los datos "in vivo" recolectados fueron utilizados para calcular el límite superior de un intervalo de confianza bilateral de 95% de la recuperación porcentual promedio, expresado por la expresión algebraica (0,66 x nuevas – 5 días), y de la supervivencia porcentual (días), expresado por la expresión (0,58 x nuevas – 5 días). El límite superior de los intervalos de confianza bilaterales de 95% para la recuperación y la supervivencia en el día 5 fue de – 4,6 y de –0,6, respectivamente, y cumplió con el requisito de ser menor que 0.
Estudio de eventos adversos (EA) relacionados con la transfusión después de que el producto ha salido al mercado
Se realizó en 6 instituciones un estudio retrospectivo a etiqueta abierta y no aleatorio de revisión de registros médicos a fin de demostrar que el índice global de EA relacionados con la transfusión en pacientes que reciben transfusiones de plaquetas con InterSol no fue mayor que el doble del índice observado en pacientes que recibieron plaquetas de aféresis almacenadas en plasma al 100% (plaquetas con plasma). El estudio clasificó las reacciones adversas a la transfusión según las definiciones descritas por “Biovigilance Component” del sistema “National Healthcare Safety Network” (NHSN). A todas las instituciones participantes se les exigió tener sistemas instalados para la observación de EA relacionados con la transfusión y para registrar cuando lo observado no era ningún EA relacionado con la transfusión. Un comité independiente de casos clínicos (CEC, Clinical Events Committee), sin ningún conocimiento del tipo de plaquetas y de la institución donde se realizó el estudio, se encargó de adjudicar los eventos registrados.
A los pacientes se les prescribieron transfusiones de plaquetas en acatamiento de la metodología normal de la institución. El tipo de plaqueta que recibió el paciente fue determinado por el inventario de la institución al momento en que se prescribió la transfusión. El personal de la institución observó al receptor de la transfusión de plaquetas en acatamiento de sus procedimientos normales. Los síntomas y las evidencias de una reacción que, posiblemente, estuvo relacionada con la transfusión se registraron utilizando los sistemas de preparación de informes existentes. En el análisis final se incluyó un total de 14 005 transfusiones procedentes de 6 instituciones donde se realizó el estudio. Se administraron un total de 4160 transfusiones de plaquetas con InterSol a un total de 1444 pacientes y se administraron 9845 transfusiones de plaquetas con plasma a un total de 2202 pacientes. Se registraron 165 reacciones adversas que fueron adjudicadas por el comité CEC. De ese número, 23 eventos fueron asociados con plaquetas con InterSol y 142 eventos fueron asociados con plaquetas con plasma.
En términos globales, un 1,13% de todas las transfusiones resultó en un EA. El porcentaje de las transfusiones de plaqueta con InterSol que resultaron en EA fue 0,55%, mientras que un 1,37% de las transfusiones de plaquetas con plasma resultaron en EA. El límite de confianza superior de 97,5% correspondiente al riesgo relativo de EA relacionados con la transfusión y asociados con plaquetas con InterSol, en relación con los correspondientes a plaquetas con plasma, fue de 0,66. Esto indica que se cumplió el objetivo del estudio de excluir la duplicación de EA relacionados con la transfusión para plaqueta con InterSol frente a plaquetas con plasma.
La mayoría de las 165 reacciones que fueron adjudicadas por el comité CEC fueron reacciones alérgicas (n=93) o reacciones febriles no hemolíticas a las transfusiones (“Febrile Non-Hemolytic Transfusions Reactions”, FNHTR, n=56), lo que significa, respectivamente, 0,66% y 0,40% del total de transfusiones. Hubo reacciones alérgicas asociadas con 0,29% de las transfusiones de plaquetas con InterSol y con 0,82% de las transfusiones de plaquetas con plasma. Los eventos FNHTR fueron asociados con 0,17% de las transfusiones de plaquetas con InterSol y con 0,50% de las transfusiones de plaquetas con plasma.
Ninguna transfusión de plaquetas con InterSol fue asociada con más de una sola reacción. Siete (7) transfusiones de plaquetas con plasma (0,07% del total de transfusiones) fueron asociadas, cada una, con dos (2) reacciones adversas independientes. Dos (2) reacciones adversas de las plaquetas con InterSol y cinco (5) reacciones adversas de las plaquetas con plasma fueron clasificadas como graves. Todas las demás reacciones fueron clasificadas como no graves. Todas las reacciones adversas fueron registradas con un efecto final “menor o sin secuelas”.
No se identificaron tendencias adversas en cuanto a seguridad después de la revisión de todos los EA por parte del Comité independiente de casos clínicos (Clinical Events Committee).

Tabla 2: Evaluaciones "in vitro"

Tabla 3: Evaluaciones "in vitro" — Plaquetas irradiadas y sin irradiar

Cómo se suministra/Manipulación y almacenamiento:
500 mL de solución esterilizada en un contenedor plástico que no es de PVC y que incluye una vía de fluido apirogéna esterilizada. El contenedor de la solución InterSol viene con una cubierta de plástico ventilada que funciona como una cubierta antipolvo para el contenedor. La cubierta antipolvo no es una barrera estéril y no es un elemento que indique la fecha de caducidad del producto InterSol.
Símbolos con sus definiciones:

Fresenius Kabi AG
61346 Bad Homburg / Germany
Tel.: +49 (0) 61 72 / 686-0
www.fresenius-kabi.com

Fenwal International Inc.
Road 357 K.M. 0.8
Maricao, Puerto Rico 00606
Importado y distribuido por:
Fresenius Kabi México S.A. de C.V.
Av. Paseo del Norte No. 5300-A,
Colonia San Juan de Ocotán,
C.P. 45010, Zapopan, Jalisco, México
Reg. No.: 0459C2021 SSA
© 2021 Fresenius Kabi AG. Todos los derechos reservados

47-23-11-648 REV: A

INDICATIONS AND USAGE

Rx only
For use with the AMICUS Separator only.
Store at Controlled Room Temperature. Protect from freezing. Avoid excessive heat. Definition of "Controlled Room Temperature":
"A temperature maintained thermostatically that encompasses the usual and customary working environment of 20° to 25°C (68° to 77°F); that results in a mean kinetic temperature calculated to be not more than 25°C; and that allows for excursions between 15°C and 30°C (59° and 86°F) that are experienced in pharmacies, hospitals, and warehouses. Provided the mean kinetic temperature remains in the allowed range, transient spikes up to 40°C are permitted as long as they do not exceed 24 hours ... The mean kinetic temperature is a calculated value that may be used as an isothermal storage temperature that simulates the non isothermal effects of storage temperature variations."
Reference: United States Pharmacopeia, General Notices. United States Pharmacopeial Convention, Inc. 12601 Twinbrook Parkway, Rockville, MD.
Dispose of waste in appropriate biohazard container or according to local regulatory requirements.

Indications and Usage:
InterSol solution is an isotonic solution designed to replace a proportion of the plasma used in the storage of AMICUS™-derived leukoreduced apheresis platelets under standard blood banking conditions. There is no direct therapeutic effect to be expected from the formulation. The solution should never be infused directly into a patient.

InterSol platelets are leukocyte-reduced apheresis platelet concentrates that are stored in a mix of 65% InterSol and 35% plasma, nominal. InterSol platelets prepared within the range of Table 1 may be stored for up to 5 days at 20-24°C, with continuous agitation.

Dosage and Administration:
InterSol solution may only be used with the AMICUS Separator System using an AMICUS Apheresis Kit with a Platelet Additive Solution (PAS) Connector. For full instructions on the use of InterSol solution with the AMICUS separator, see the AMICUS Operator’s Manual.

Prior to use of InterSol solution, check the plastic container for leaks by squeezing the bag firmly. If leaks are found, discard solution.

To connect the InterSol solution to the AMICUS Apheresis Kit:
1) Close the clamp on the PAS Connector line.
2) Remove the protective cap from the membrane port on the InterSol solution container.
3) Insert the spike on the PAS Connector line into the membrane port on the InterSol solution container until firmly seated.
4) For the addition of InterSol solution to the platelet product, follow the instructions provided in the AMICUS Separator Operator’s Manual.

Dosage Forms and Strengths:
InterSol solution is provided as a 500 mL sterile and non-pyrogenic solution in a non-PVC plastic container with a sterile and non-pyrogenic fluid path. Each 100 mL contains 305 mg Dibasic Sodium Phosphate, Anhydrous, USP; 93 mg Monobasic Sodium Phosphate, Monohydrate, USP; 318 mg Sodium Citrate, Dihydrate, USP; 442 mg Sodium Acetate, Trihydrate, USP; 452 mg Sodium Chloride, USP; Water for Injection, USP quantity sufficient.

Contraindications:
InterSol solution is added to AMICUS-derived leukoreduced platelet concentrates after the apheresis procedure is complete. It is not for direct intravenous infusion. There are no known contraindications associated with the use of InterSol solution for the preparation of InterSol platelets.

Warnings and Precautions:

- InterSol solution is NOT FOR DIRECT INTRAVENOUS INFUSION.
- Do not use if particulate matter is present or if the solution is cloudy.
- Do not use if the container is damaged, leaking or if there is any visible sign of deterioration.
- Do not vent.
- Do not reuse. Discard unused or partially used InterSol solution.
- Protect from sharp objects.
- Verify that the InterSol solution has been securely attached to the PAS Connector line to avoid disconnection and leaks.

Adverse Reactions:
InterSol solution is added to AMICUS-derived leukoreduced platelet concentrates after the apheresis procedure is complete. It is not for direct intravenous infusion. InterSol solution is not expected to cause adverse events other than those normally associated with platelet transfusion.

Drug Abuse / Dependence:
InterSol solution is used as a storage solution for platelet concentrates and has no pharmacological effect.

Overdosage:
InterSol solution is used as a storage solution for platelet concentrates and it is not for direct intravenous infusion.

Description:
InterSol solution is an isotonic solution designed to replace a proportion of the plasma used in the storage of platelets. The solution contains constituents that are naturally occurring components present in many cellular systems: sodium acetate as a nutrient, sodium citrate to prevent platelet clumping and activation, sodium phosphate for buffering and sodium chloride for osmolarity. InterSol solution does not have a pharmacological effect in vivo, but rather acts to provide the appropriate environment and nutrients in lieu of a portion of the plasma normally used for the storage of platelets.

Clinical Pharmacology:
InterSol solution is used as a storage solution for platelet concentrates and it is not for direct intravenous infusion. This solution has no pharmacological effect.

Clinical Studies:

In Vitro Biochemical and Functional Evaluations
InterSol platelet concentrates (n=70) prepared using the AMICUS separator and stored for 5 days showed a median and mean pH value on Day 5 of 7.2 and 7.2 ± 0.1 (range: 6.9-7.5), respectively, with a lower non-parametric 95%/95% tolerance limit of 6.9.

Supplemental in vitro assessments of InterSol platelets and AMICUS-derived leukoreduced platelets stored in 100% plasma are presented in Table 2.

InterSol platelets irradiated (n=18) at either 2500 or 2800 cGray (dependent on site procedures) were compared to non-irradiated InterSol platelets. At the end of storage on Day 5 the platelet yields of the irradiated products were concentrated between 2.5 x 10^11 to 3.5 x 10^11 and included one product with a yield less than2.5 x 10^11 and two products with yields greater than 3.5 x 10^11. In vitro testing is not predictive of in vivo performance, which was not evaluated. Summary statistics are presented in Table 3.

In Vivo Recovery and Survival in Healthy Subjects

In vivo evaluation of InterSol platelets at Day 5 (n=33) compared to a fresh platelet control resulted in a mean percent recovery of 46.4 ± 11.9 percent and 58.0 ± 10.7 percent and mean survival of 5.7 ± 1.4 days and 8.0 ± 1.4 days, respectively. The in vivo data collected were used to calculate the upper limit of a two-sided 95% confidence interval of the mean percent recovery of the algebraic expression (0.66 x Fresh – 5 Day), and of the mean percent survival (days) of the algebraic expression (0.58 x Fresh – 5 Day). The upper bound of the two-sided 95% confidence intervals for recovery and survival on Day 5 was –4.6 and –0.6 respectively and met the requirement of less than 0.

Post-Market Transfusion-Related Adverse Events (AE) Study

An open label, non-randomized, retrospective medical record review study was performed in 6 centers to demonstrate that the overall rate of transfusion-related AEs in patients receiving InterSol Platelet transfusions was not more than double the rate in patients receiving apheresis platelets stored in 100% plasma (Plasma Platelets). The study categorized adverse transfusion reactions according to the definitions outlined by the Biovigilance Component of the National Healthcare Safety Network (NHSN) System. All sites that participated were required to have systems in place to observe transfusion-related AEs and to record when no transfusion-related AE was observed. An independent Clinical Events Committee (CEC) blinded to platelet type and study site adjudicated the reported events.

Patients were prescribed platelet transfusions per each site’s standard practice. The type of platelet unit the patient received was based on the site’s inventory at the time the transfusion was ordered. Site personnel observed the platelet transfusion recipient following their standard procedures. Signs and symptoms of a potential transfusion-related reaction were noted using existing reporting systems. A total of 14,005 transfusions from 6 study sites were included in the final analysis. A total of 4,160 InterSol Platelet transfusions were given to a total of 1,444 patients, and 9,845 Plasma Platelet transfusions were given to 2,202 patients. There were 165 CEC-adjudicated adverse reactions reported. Of those, 23 events were associated with InterSol Platelets and 142 events were associated with Plasma Platelets.

Overall, 1.13% of all transfusions resulted in an AE. The percentage of InterSol Platelet transfusions which led to AEs was 0.55%, while 1.37% of Plasma Platelet transfusions resulted in AEs. The 97.5% upper confidence limit for the relative risk of transfusion-related AE associated with InterSol Platelets relative to Plasma Platelets was 0.66, indicating that the study objective of ruling out a doubling of transfusion-related AEs for InterSol vs. Plasma Platelets was met.

The majority of the 165 CEC-adjudicated reactions were Allergic (n=93) or Febrile Non-Hemolytic Transfusions Reactions (FNHTR, n=56), at 0.66% and 0.40% of total transfusions, respectively. There were allergic reactions associated with 0.29% of InterSol Platelet transfusions and 0.82% of Plasma Platelet transfusions. FNHTR events were associated with 0.17% of InterSol Platelet transfusions and 0.50% of Plasma Platelet transfusions.

No InterSol Platelet transfusion was associated with more than one reaction. Seven (7) Plasma Platelet transfusions (0.07% of total transfusions) were associated with two separate adverse reactions each. Two (2) InterSol Platelet and five (5) Plasma Platelet adverse reactions were classified as severe. All other reactions were classified as non-severe. All adverse reactions were reported with an outcome of “Minor or No Sequelae”.

No adverse safety trends were identified after review of all the AEs by the independent Clinical Events Committee.

How Supplied/Storage and Handling:
500 mL sterile solution in a non-PVC plastic container with a sterile, non-pyrogenic fluid path. The InterSol solution container is supplied in a vented plastic overwrap covering that serves as a dust cover for the container. The dust cover is not a sterility barrier and is not an element that defines the expiration date of the InterSol product.

© 2021 Fresenius Kabi AG. All rights reserved.

Fresenius Kabi AG
61346 Bad Homburg / Germany
Tel.: +49 (0) 61 72 / 686-0
www.fresenius-kabi.com

PACKAGE/LABEL PRINCIPAL DISPLAY PANEL

L6B7850
NDC No. 0942-9603-12
Solamente Rx
500 mL
Solución InterSol Solución aditiva para plaquetas 3
Para ser usada exclusivamente con el separador AMICUS. Almacenar a temperatura ambiente controlada. Proteger de la congelación. Evitar el calor excesivo. Deseche la porción no utilizada. Cada 100 mL contienen 305 mg de fosfato de sodio dibásico, anhidro, USP; 93 mg de fosfato de sodio monobásico, monohidratado, USP; 318 mg de citrato de sodio, dihidratado, USP; 442 mg de acetato de sodio, trihidratado, USP; 452 mg de cloruro de sodio, USP; agua para inyección, USP, en cantidad suficiente.
NO PARA INFUSIÓN INTRAVENOSA DIRECTA.
Fabricado para
Fresenius Kabi AG
61346 Bad Homburg / Germany
Tel.: +49 (0) 61 72 / 686-0

Fabricado por
Fenwal International Inc.
Road 357 K.M. 0.8
Maricao, Puerto Rico 00606
Made in US
Importado y Distribuido por:
Uruguay BIOERIX SA
Simón Bolívar 1472-
Tel/Fax 27081624
Dirección Técnica: Q.F. Mariela Ricca
Importado y distribuido por:
Fresenius Kabi México S.A. de C.V.

Av. Paseo del Norte No. 5300-A,
Colonia San Juan de Ocotán,
C.P. 45010, Zapopan, Jalisco, México
Reg. No.: 0459C2021 SSA

Importado y distribuido por:

Fresenius Kabi Colombia S.A.S.

Avenida Carrera 7° No. 155c-20 Piso 40

Bogotá, Colombia

Phone: +57 (1) 7 56 04 04

Reg. San. No.

INVIMA 2021DM-0006825-R1

47-17-11-646 REV: A

L6B7850
NDC No. 0942-9603-12
Rx Only
500 mL
InterSol Solution Platelet Additive Solution 3
For use with the AMICUS separator only. Store at Controlled Room Temperature. Protect from freezing. Avoid excessive heat.

Discard unused portion. Each 100 mL contains 305 mg Dibasic Sodium Phosphate, Anhydrous, USP; 93 mg Monobasic Sodium Phosphate, Monohydrate, USP; 318 mg Sodium Citrate, Dihydrate, USP; 442 mg Sodium Acetate, Trihydrate, USP; 452 mg Sodium Chloride, USP; Water for Injection, USP quantity sufficient.

NOT FOR DIRECT INTRAVENOUS INFUSION.

Manufacturer
Fresenius Kabi AG
61346 Bad Homburg / Germany
Tel.: +49 (0) 61 72 / 686-0

Manufacturing facility/
Manufacture by
Fenwal International Inc.
Road 357 K.M. 0.8
Maricao, Puerto Rico 00606
Made in US
Imported and distributed by:
Uruguay BIOERIX SA
Simón Bolívar 1472-
Tel/Fax 27081624
Dirección Técnica: Q.F. Mariela Ricca
Imported and distributed by:
Fresenius Kabi México S.A. de C.V.
Av. Paseo del Norte No. 5300-A,
Colonia San Juan de Ocotán,
C.P. 45010, Zapopan, Jalisco, México
Reg. No.: 0459C2021 SSA

Imported and distributed by:

Fresenius Kabi Colombia S.A.S.

Avenida Carrera 7° No. 155c-20 Piso 40

Bogotá, Colombia

Phone: +57 (1) 7 56 04 04

Reg. San. No.

INVIMA 2021DM-0006825-R1

47-17-11-646 REV: A